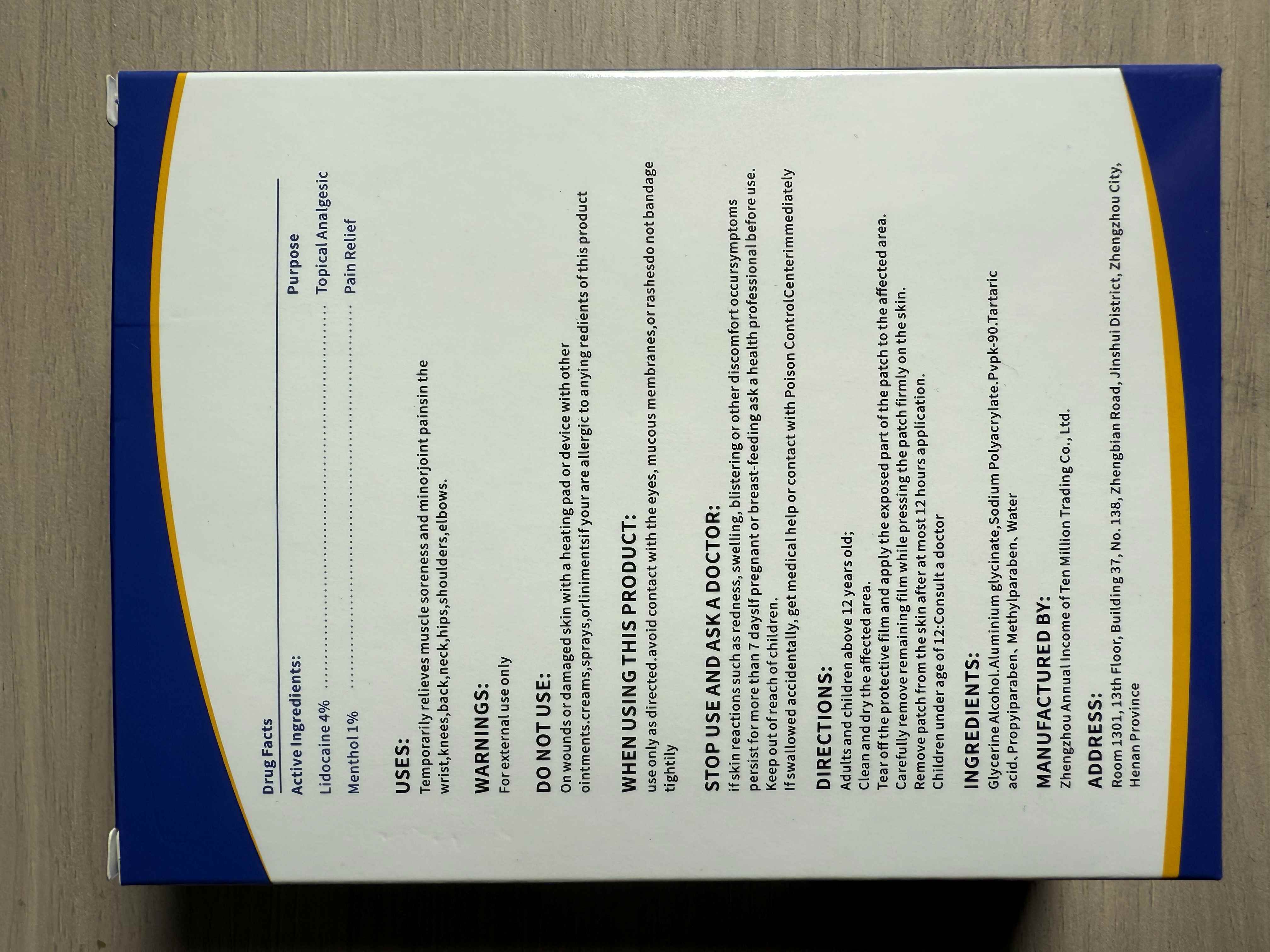 DRUG LABEL: 4% Lidocaine Patches
NDC: 85593-010 | Form: PATCH
Manufacturer: Guangzhou ChuanMa International Trading Co.,Ltd.
Category: otc | Type: HUMAN OTC DRUG LABEL
Date: 20250902

ACTIVE INGREDIENTS: MENTHOL 1 g/100 g; LIDOCAINE 4 g/100 g
INACTIVE INGREDIENTS: TARTARIC ACID; POVIDONE K90; DIHYDROXYALUMINUM AMINOACETATE; METHYLPARABEN; PROPYLPARABEN; GLYCERIN

ACTIVE INGREDIENT

Lidocaine 4%4
Menthol 1%

INACTIVE INGREDIENT

INGREDIENTS:
Glycerine Alcohol.Aluminium glycinate,Sodium Polyacrylate.Pvpk-90.Tartaricacid、Propyiparaben、Methylparaben、Water

PURPOSE

USES:Temporarily relieves muscle soreness and minorjoint painsin thewrist,knees,back,neck,hips,shoulders,elbows.

WARNINGS:For external use only

INDICATIONS AND USAGE

use only as directed.avoid contact with the eyes, mucous membranes,orrashesdo not bandagetightily

DOSAGE AND ADMINISTRATION

Adults and children above 12 years old;

Clean and dry the affected area.Tear off the protective film and apply the exposed part ofthe patch to the affected area.

Carefullyremove remainingfilm while pressing the patch firmly on the skin.Remove patch from the skin after at most 12 hours application.Children under age of 12:Consult a doctor

Keep out of reach ofchildren.
lf swallowed accidentally, get medical help or contact with Poison ControlCenterimmediately

DO NOT USE:
On wounds or damaged skin with a heating pad or device with otherointments.creams,sprays,orlinimentsifyour are allergic to anying redients ofthis product